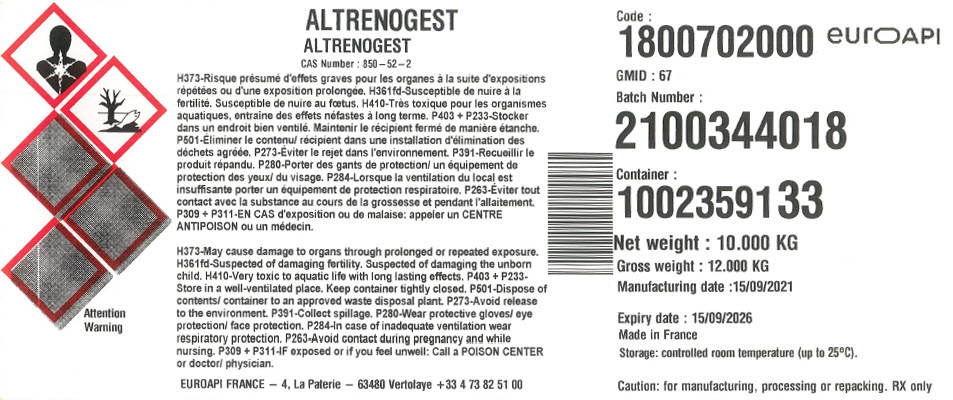 DRUG LABEL: Altrenogest
NDC: 82298-122 | Form: POWDER
Manufacturer: EUROAPI France
Category: other | Type: BULK INGREDIENT - ANIMAL DRUG
Date: 20220316

ACTIVE INGREDIENTS: Altrenogest 1 kg/1 kg

ALTRENOGEST

PRINCIPAL DISPLAY PANEL - Shipping Label

ALTRENOGEST
CAS Number : 850–52–2

Attention
Warning

H373-May cause damage to organs through prolonged or repeated exposure.
H361fd-Suspected of damaging fertility. Suspected of damaging the unborn
child. H410-Very toxic to aquatic life with long lasting effects. P403 + P233-
Store in a well-ventilated place. Keep container tightly closed. P501-Dispose of
contents/ container to an approved waste disposal plant. P273-Avoid release
to the environment. P391-Collect spillage. P280-Wear protective gloves/ eye
protection/ face protection. P284-In case of inadequate ventilation wear
respiratory protection. P263-Avoid contact during pregnancy and while
nursing. P309 + P311-IF exposed or if you feel unwell: Call a POISON CENTER
or doctor/ physician.

EUROAPI FRANCE – 4, La Paterie – 63480 Vertolaye +33 4 73 82 51 00

Code :
1800702000

euroAPI

GMID : 67

Batch Number :
2100344018

Container :
1002359133

Net weight : 10.000 KG
Gross weight : 12.000 KG
Manufacturing date :15/09/2021

Expiry date : 15/09/2026
Made in France
Storage: controlled room temperature (up to 25°C).

Caution: for manufacturing, processing or repacking. RX only